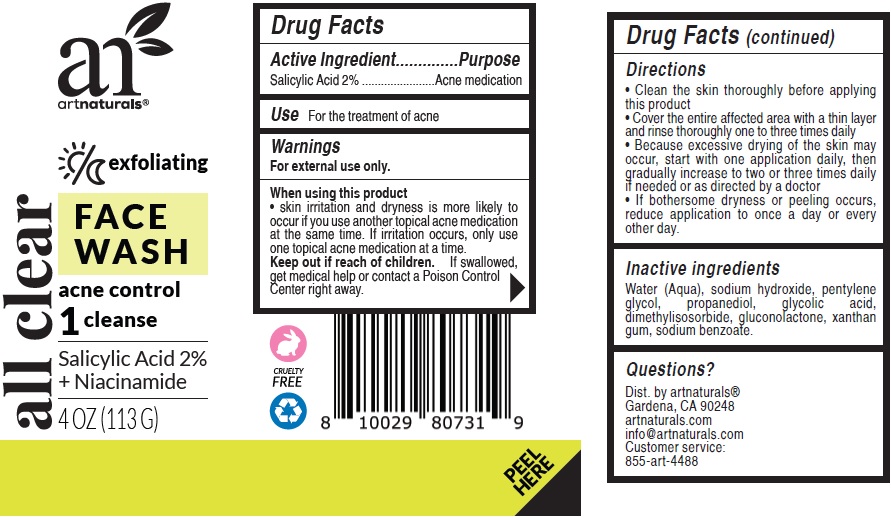 DRUG LABEL: all clear exfoliating face wash
NDC: 78706-006 | Form: PASTE
Manufacturer: Virgin Scent Inc.
Category: otc | Type: HUMAN OTC DRUG LABEL
Date: 20211221

ACTIVE INGREDIENTS: SALICYLIC ACID 20 mg/1 g
INACTIVE INGREDIENTS: WATER; SODIUM HYDROXIDE; PENTYLENE GLYCOL; PROPANEDIOL; GLYCOLIC ACID; DIMETHYL ISOSORBIDE; GLUCONOLACTONE; XANTHAN GUM; SODIUM BENZOATE

all clear exfoliating face wash

Active Ingredient

Salicylic Acid 2%

Purpose

Acne medication

Use

For the treatment of acne

Warnings

For external use only.

When using this product

• skin irritation and dryness is more likely to occur if you use another topical acne medication at the same time. If irritation occurs, only use one topical acne medication at a time.

Keep out if reach of children.

If swallowed, get medical help or contact a Poison Control Center right away.

Directions

• Clean the skin thoroughly before applying this product
• Cover the entire affected area with a thin layer and rinse thoroughly one to three times daily
• Because excessive drying of the skin may occur, start with one application daily, then gradually increase to two or three times daily if needed or as directed by a doctor
• If bothersome dryness or peeling occurs, reduce application to once a day or every

Inactive Ingredients

Water (Aqua), sodium hydroxide, pentylene glycol, propanediol, glycolic acid, dimethylisosorbide, gluconolactone, xanthan gum, sodium benzoate

Questions?

info@artnaturals.com
Customer service: 855-art-4488